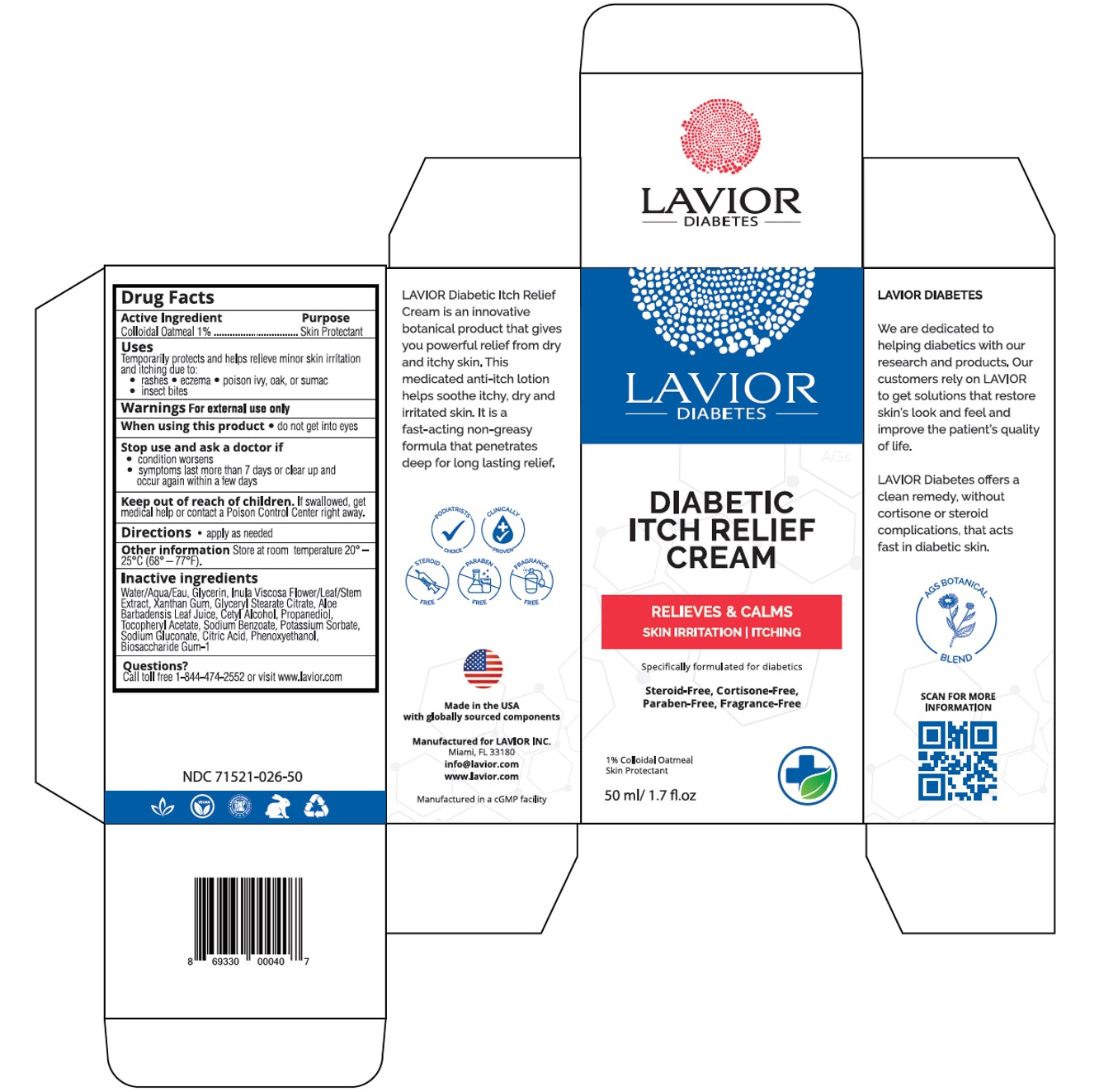 DRUG LABEL: Diabetic Itch Relief Cream
NDC: 71521-026 | Form: CREAM
Manufacturer: Lavior Pharma Inc
Category: otc | Type: HUMAN OTC DRUG LABEL
Date: 20241022

ACTIVE INGREDIENTS: OATMEAL 1 g/100 g
INACTIVE INGREDIENTS: SODIUM BENZOATE; GLYCERYL STEARATE CITRATE; DITTRICHIA VISCOSA WHOLE; GLYCERIN; ALOE VERA LEAF; XANTHAN GUM; .ALPHA.-TOCOPHEROL ACETATE, D-; CITRIC ACID MONOHYDRATE; POTASSIUM SORBATE; CETYL ALCOHOL; BIOSACCHARIDE GUM-1; SODIUM GLUCONATE; PROPANEDIOL

Active Ingredient

Colloidal Oatmeal 1%......................Skin Protectant

Purpose

Skin Protectant

Uses

Temporarily protects and helps relieve minor skin irritation and itching due to:

• rashes

• eczema

• poison ivy, oak, or sumac

• insect bites

Warnings

For external use only

When using this product

- do not get into eyes

Stop use and ask a doctor if

• condition worsens

• symptoms last more than 7 days or clear up and occur again within a few days

Keep out of reach of children

If swallowed, get medical help or contact a Poison Control Center right away.

Directions

- apply as needed

Other Information

Store at room temperature 20° – 25°C (68° – 77°F).

Inactive Ingredients

Aqua, Glycerin, Inula Viscosa Flower/Leaf/Stem Extract, Xanthan Gum, Glyceryl Stearate Citrate, Aloe Barbadensis Leaf Juice, Propanediol-1,3, Cetyl Alcohol, Sodium Benzoate, Potassium Sorbate, Biosaccharide Gum-1, Tocopheryl Acetate (Vitamin E), Sodium Gluconate, Citric Acid.

Questions?

Call (305) 627-3680 or visit www.lavior.com